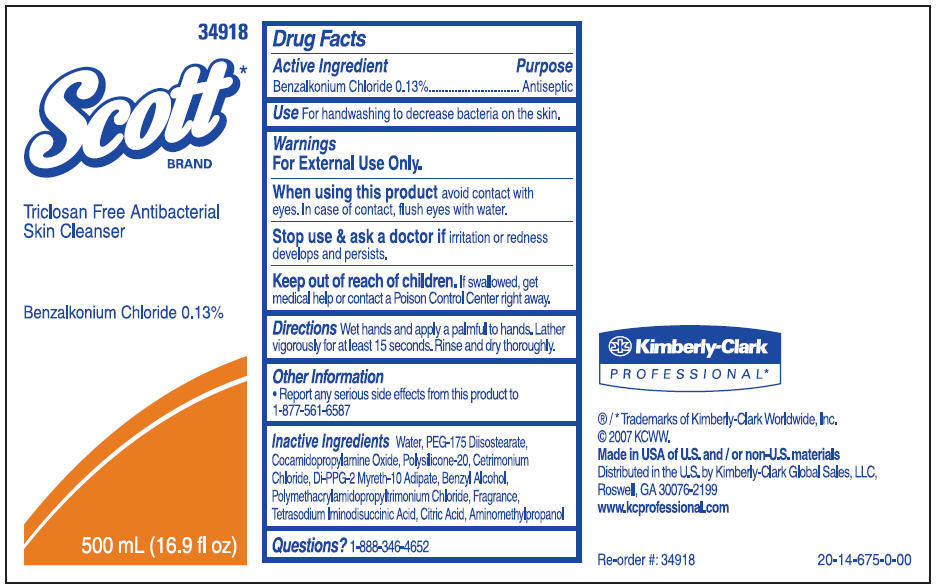 DRUG LABEL: Scott Triclosan Free Antibacterial Skin Cleanser
NDC: 55118-555 | Form: SOLUTION
Manufacturer: Kimberly-Clark Corporation
Category: otc | Type: HUMAN OTC DRUG LABEL
Date: 20141104

ACTIVE INGREDIENTS: Benzalkonium Chloride 0.13 g/100 mL
INACTIVE INGREDIENTS: WATER; COCAMIDOPROPYLAMINE OXIDE; CETRIMONIUM CHLORIDE; BENZYL ALCOHOL; CITRIC ACID MONOHYDRATE; AMINOMETHYLPROPANOL

Scott Triclosan Free Antibacterial Skin Cleanser

Drug Facts

Active Ingredient

Benzalkonium Chloride 0.13%

Purpose

Antiseptic

Use

For handwashing to decrease bacteria on the skin.

Warnings

For External Use Only.

When using this product avoid contact with eyes. In case of contact, flush eyes with water.

Stop use & ask a doctor if irritation or redness develops and persists.

Keep out of reach of children. If swallowed, get medical help or contact a Poison Control Center right away.

Directions

Wet hands and apply a palmful to hands. Lather vigorously for at least 15 seconds. Rinse and dry thoroughly.

Other Information

- Report any serious side effects from this product to 1-877-561-6587

Inactive Ingredients

Water, PEG-175 Diisostearate, Cocamidopropylamine Oxide, Polysilicone-20, Cetrimonium Chloride, Di-PPG-2 Myreth-10 Adipate, Benzyl Alcohol, Polymethacrylamidopropyltrimonium Chloride, Fragrance, Tetrasodium Iminodisuccinic Acid, Citric Acid, Aminomethylpropanol

Questions?

1-888-346-4652

Distributed in the U.S. by Kimberly-Clark Global Sales, LLC,
Roswell, GA 30076-2199

PRINCIPAL DISPLAY PANEL - 500 mL Bottle Label

34918

Scott*
BRAND

Triclosan Free Antibacterial
Skin Cleanser

Benzalkonium Chloride 0.13%

500 mL (16.9 fl oz)